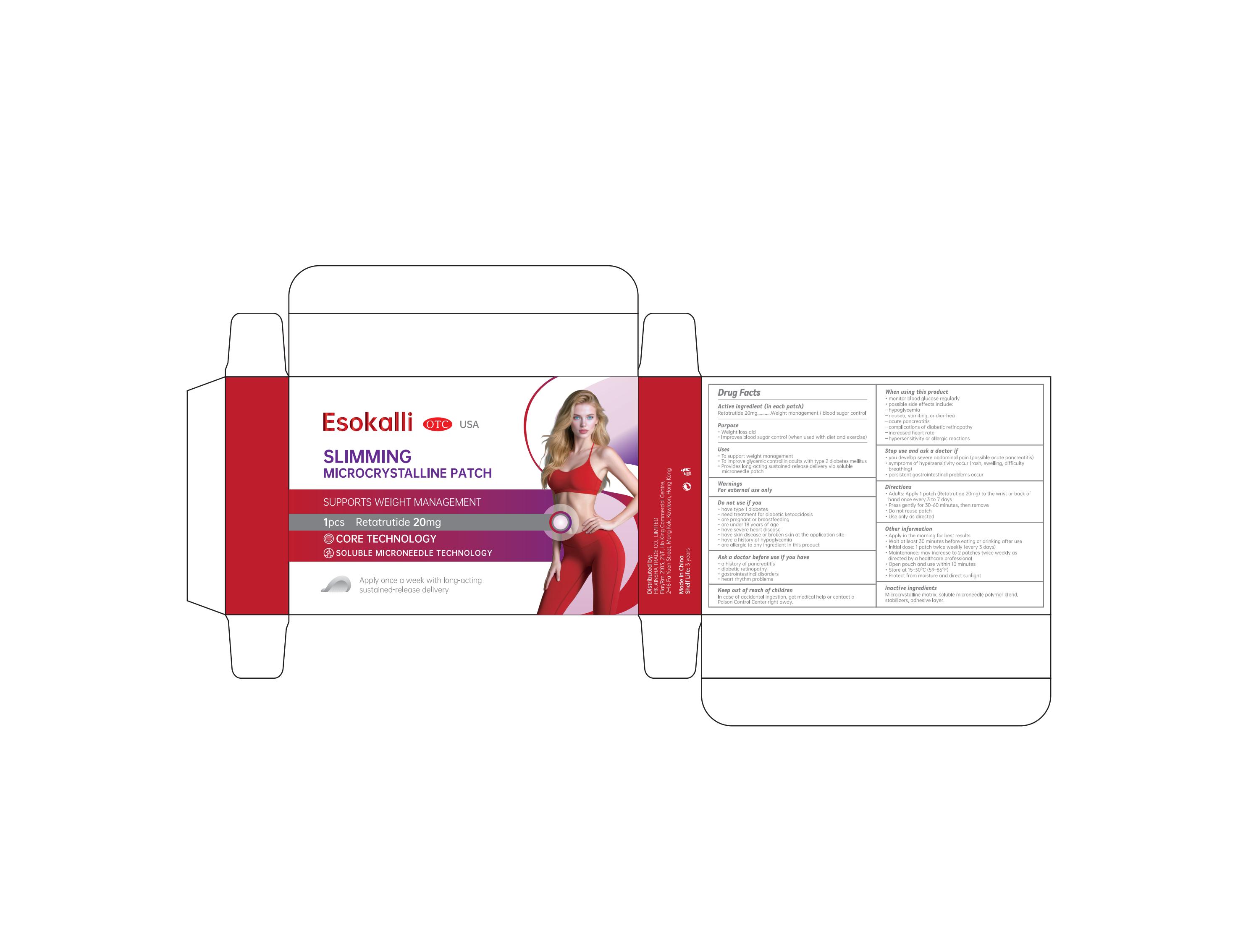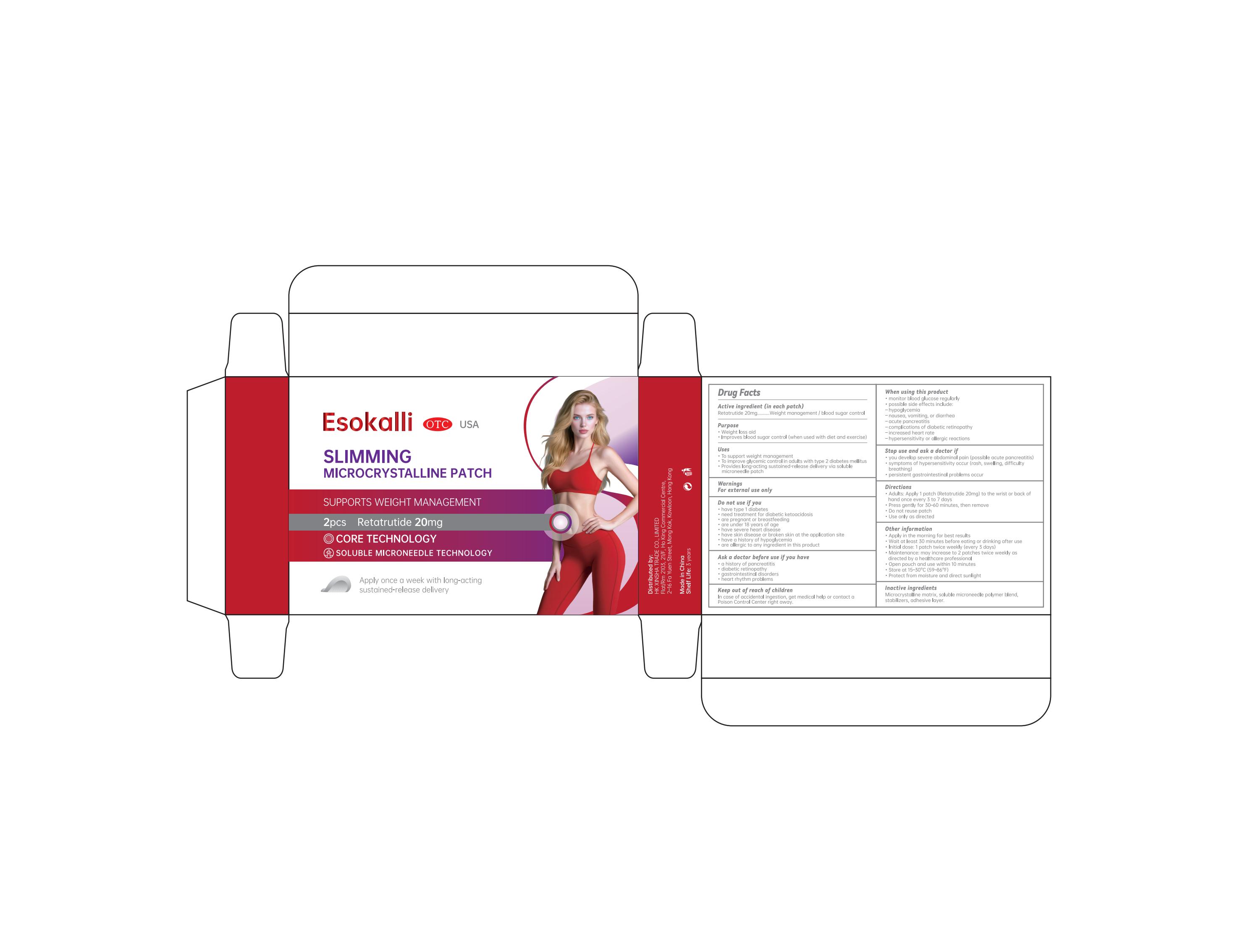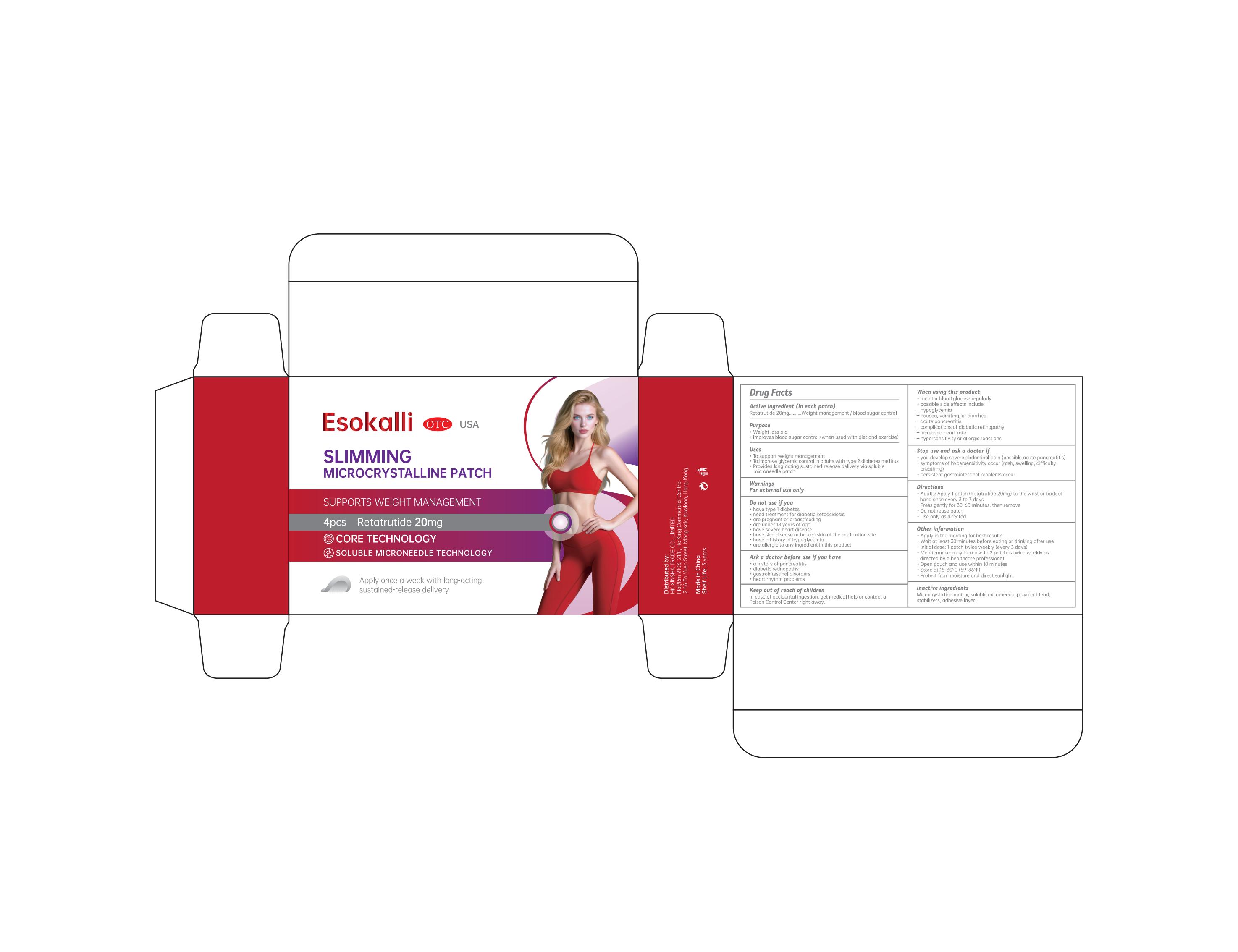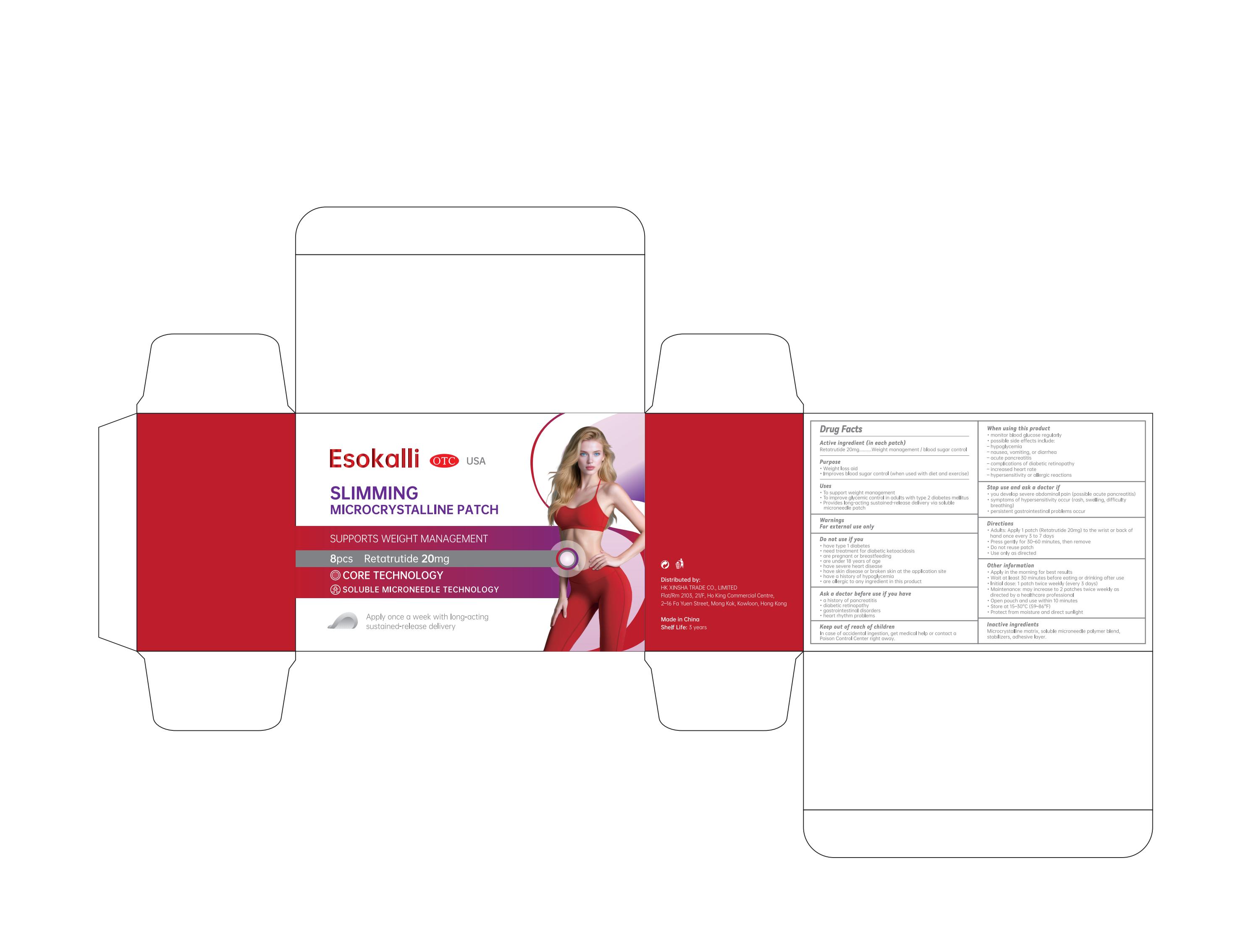 DRUG LABEL: Esokalli Slimming microcrystalline patch
NDC: 84778-082 | Form: PATCH
Manufacturer: Guangzhou Yixin Cross-border E-commerce Co., Ltd.
Category: otc | Type: HUMAN OTC DRUG LABEL
Date: 20250901

ACTIVE INGREDIENTS: RETATRUTIDE 20 mg/100 mg
INACTIVE INGREDIENTS: CELLULOSE, MICROCRYSTALLINE; POLYVINYL ALCOHOL, UNSPECIFIED; SUCROSE; DIMETHICONE, UNSPECIFIED

Active ingredient (in each patch)

Retatrutide 20 mg ……………………………. Weight management / blood sugar control

Purpose

Weight loss aid
Improves blood sugar control (when used with diet and exercise)

Uses

To support weight management
To improve glycemic control in adults with type 2 diabetes mellitus
Provides long-acting sustained-release delivery via soluble microneedle patch

Warnings

For external use only

Dosage and administration

• Apply one transdermal patch containing 20 mg Retatrutide to the wrist or the back of the hand.
• Leave the patch in place for 30 to 60 minutes, then remove.
• Administer once every 3 to 7 days.
• Do not reuse a patch.
• Use only as directed.

Do not use if you

• have type 1 diabetes

• need treatment for diabetic ketoacidosis

• are pregnant or breastfeeding

• are under 18 years of age

• have severe heart disease

• have skin disease or broken skin at the application site

• have a history of hypoglycemia

• are allergic to any ingredient in this product

When using this product

• monitor blood glucose regularly

• possible side effects include:

– hypoglycemia

– nausea, vomiting, or diarrhea

– acute pancreatitis

– complications of diabetic retinopathy

– increased heart rate

– hypersensitivity or allergic reactions

Stop use and ask a doctor if

• you develop severe abdominal pain (possible acute pancreatitis)

• symptoms of hypersensitivity occur (rash, swelling, difficulty breathing)

• persistent gastrointestinal problems occur

Keep out of reach of children.

In case of accidental ingestion, get medical help or contact a Poison Control Center right away.

Inactive ingredients

Microcrystalline matrix, soluble microneedle polymer blend, stabilizers, adhesive layer.